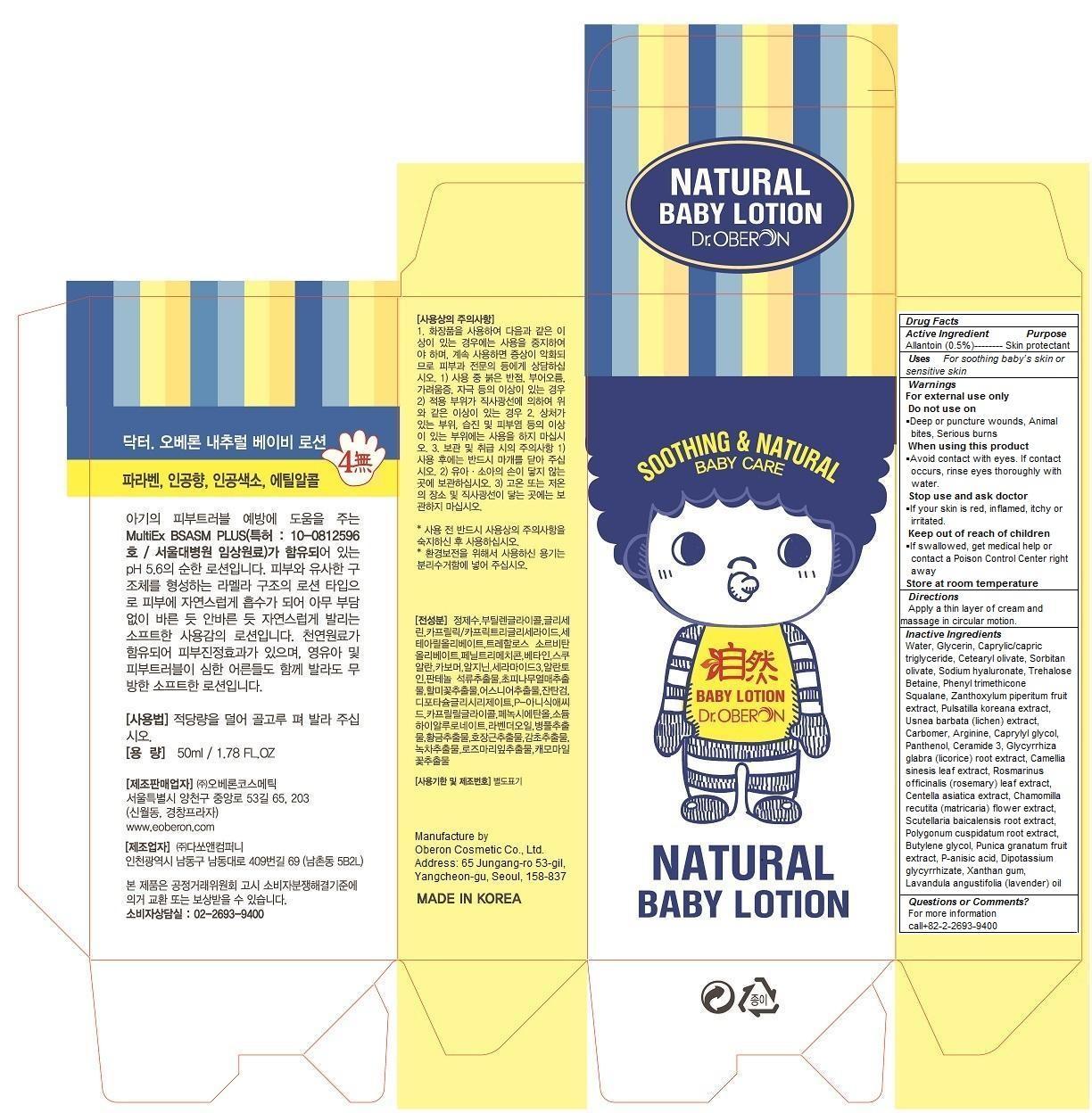 DRUG LABEL: DR. OBERON NATURAL BABY
NDC: 52891-103 | Form: LOTION
Manufacturer: Oberon Cosmetic Co., Ltd.
Category: otc | Type: HUMAN OTC DRUG LABEL
Date: 20140629

ACTIVE INGREDIENTS: ALLANTOIN 0.5 1/50 mL
INACTIVE INGREDIENTS: water; Glycerin; CAPRYLIC/CAPRIC/SUCCINIC TRIGLYCERIDE; CETEARYL OLIVATE; SORBITAN OLIVATE; PEG-9 DIGLYCIDYL ETHER/SODIUM HYALURONATE CROSSPOLYMER; Trehalose; Betaine; PHENYL TRIMETHICONE; Squalane; ZANTHOXYLUM PIPERITUM FRUIT PULP; PULSATILLA KOREANA WHOLE; USNEA BARBATA; CARBOMER 1342; Arginine; CAPRYLYL GLYCOL; Panthenol; CERAMIDE 3; GLYCYRRHIZA GLABRA; CAMELLIA SINENSIS FLOWER; ROSMARINUS OFFICINALIS FLOWER; CENTELLA ASIATICA; MATRICARIA CHAMOMILLA FLOWERING TOP OIL; SCUTELLARIA BAICALENSIS ROOT; POLYGONUM CUSPIDATUM ROOT; BUTYLENE GLYCOL; PUNICA GRANATUM WHOLE; P-anisic acid; DIPOTASSIUM GLUCOSE-6-PHOSPHATE; XANTHAN GUM; LAVANDULA ANGUSTIFOLIA WHOLE

DR. OBERON NATURAL BABY LOTION